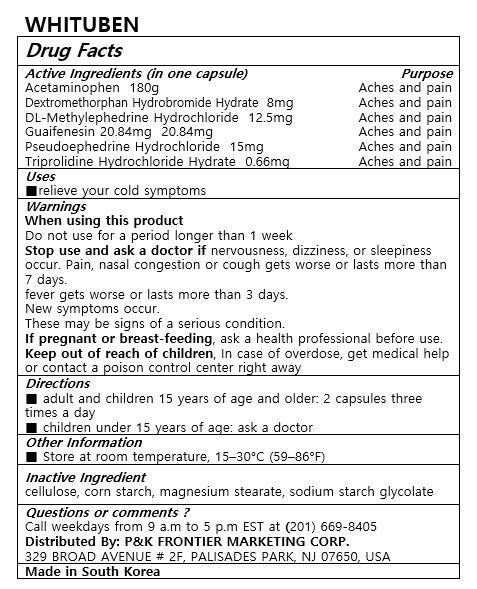 DRUG LABEL: WHITUBEN
NDC: 72689-0037 | Form: CAPSULE
Manufacturer: OASIS TRADING
Category: otc | Type: HUMAN OTC DRUG LABEL
Date: 20190318

ACTIVE INGREDIENTS: ACETAMINOPHEN 180 mg/1 1; GUAIFENESIN 20.84 mg/1 1; PSEUDOEPHEDRINE HYDROCHLORIDE 15 mg/1 1; METHYLEPHEDRINE HYDROCHLORIDE, (+/-)- 12.5 mg/1 1; TRIPROLIDINE HYDROCHLORIDE 0.66 mg/1 1; DEXTROMETHORPHAN HYDROBROMIDE 8 mg/1 1
INACTIVE INGREDIENTS: STARCH, CORN

ACTIVE INGREDIENT

Acetaminophen 180mg
Dextromethorphan Hydrobromide Hydrate 8mg
DL-Methylephedrine Hydrochloride 12.5mg
Guaifenesin 20.84mg
Pseudoephedrine Hydrochloride 15mg
Triprolidine Hydrochloride Hydrate 0.66mg

PURPOSE

relieve your cold symptoms

Keep out of reach of children

INDICATIONS AND USAGE

■ adult and children 15 years of age and older: 2 capsules three times a day
■ children under 15 years of age: ask a doctor

Warnings
When using this product
Do not use for a period longer than 1 weeks
Stop use and ask a doctor if nervousness, dizziness, or sleepness occur. Pain, nasal congestion or cough gets worse or lasts more than 7 days.
fever gets worse or lasts more than 3 days
New symptoms occur
These may be signs of a serious condition.
If pregnant or breast-feeding, ask a health professional before use.
Keep out of reach of children, In case of overdose, get medical help or contact a poison control center right away

INACTIVE INGREDIENT

cellulose, corn starch, magnesium stearate, sodium starch glycolate

DOSAGE AND ADMINISTRATION

For oral use only